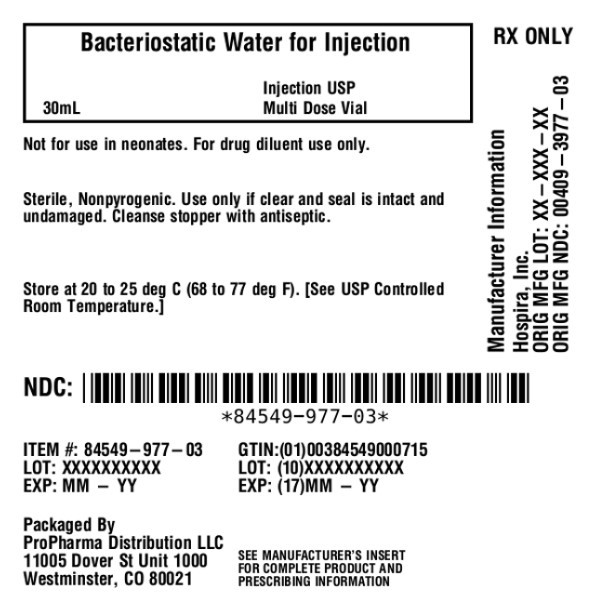 DRUG LABEL: Bacteriostatic Water
NDC: 84549-977 | Form: INJECTION, SOLUTION
Manufacturer: ProPharma Distribution
Category: prescription | Type: HUMAN PRESCRIPTION DRUG LABEL
Date: 20251104

ACTIVE INGREDIENTS: WATER 1 mL/1 mL
INACTIVE INGREDIENTS: BENZYL ALCOHOL 9 mg/1 mL

BACTERIOSTATIC WATER Rx only
for Injection, USP

Multiple-dose Vial

WARNING:

NOT FOR USE IN NEONATES.

DESCRIPTION

The following preparation is designed solely for parenteral use only after addition of drugs that require dilution or must be dissolved in an aqueous vehicle prior to injection.

Bacteriostatic Water for Injection, USP is a sterile, nonpyrogenic preparation of water for injection containing 0.9% (9 mg/mL) or 1.1% (11 mg/mL) of benzyl alcohol added as a bacteriostatic preservative. It is supplied in a multiple-dose container from which repeated withdrawals may be made to dilute or dissolve drugs for injection. The pH is 5.7 (4.5 to 7.0).

Water for Injection, USP is chemically designated H2O.

The semi-rigid vial is fabricated from a specially formulated polyolefin. It is a copolymer of ethylene and propylene. The safety of the plastic has been confirmed by tests in animals according to USP biological standards for plastic containers. The container requires no vapor barrier to maintain the proper labeled volume.

CLINICAL PHARMACOLOGY

Water is an essential constituent of all body tissues and accounts for approximately 70% of total body weight. Average normal adult daily requirement ranges from two to three liters (1.0 to 1.5 liters each for insensible water loss by perspiration and urine production).

Water balance is maintained by various regulatory mechanisms. Water distribution depends primarily on the concentration of electrolytes in the body compartments and sodium (Na^+) plays a major role in maintaining physiologic equilibrium.

The small volume of fluid provided by Bacteriostatic Water for Injection, USP when used only as a pharmaceutic aid for diluting or dissolving drugs for parenteral injection, is unlikely to exert a significant effect on fluid balance except possibly in very small infants.

INDICATIONS AND USAGE

This parenteral preparation is indicated only for diluting or dissolving drugs for intravenous, intramuscular or subcutaneous injection, according to instructions of the manufacturer of the drug to be administered.

CONTRAINDICATIONS

Due to the potential toxicity of benzyl alcohol in neonates, solutions containing benzyl alcohol must not be used in this patient population.

Parenteral preparations with benzyl alcohol should not be used for fluid replacement.

Parenteral preparations containing benzyl alcohol should not be used in epidural or spinal anesthesia procedures.

Bacteriostatic Water for Injection, USP must be made approximately isotonic prior to use.

WARNINGS

Benzyl alcohol, a preservative in Bacteriostatic Water for Injection, USP has been associated with toxicity in neonates. Data are unavailable on the toxicity of other preservatives in this age group. Where water is required for preparing or diluting medications for use in neonates, only preservative-free Sterile Water for Injection should be used.

Intravenous administration of Bacteriostatic Water for Injection without a solute may result in hemolysis.

PRECAUTIONS

Do not use Bacteriostatic Water for Injection, USP for intravenous injection unless the osmolar concentration of additives results in an approximate isotonic admixture.

Consult the manufacturer's instructions for choice of vehicle, appropriate dilution or volume for dissolving the drugs to be injected, including the route and rate of injection.

Inspect reconstituted (diluted or dissolved) drugs for clarity (if soluble) and freedom from unexpected precipitation or discoloration prior to administration.

Pregnancy:Animal reproduction studies have not been conducted with Bacteriostatic Water for Injection. It is also not known whether Bacteriostatic Water for Injection containing additives can cause fetal harm when administered to a pregnant woman or can affect reproduction capacity. Bacteriostatic Water for Injection, USP containing additives should be given to a pregnant woman only if clearly needed.

Pediatric Use

The safety and effectiveness of Bacteriostatic Water for Injection, USP have not been established in pediatric patients. Due to the potential for toxicity, solutions containing benzyl alcohol should not be used in neonates.

Drug Interactions

Some drugs for injection may be incompatible in a given vehicle, or when combined in the same vehicle or in a vehicle containing benzyl alcohol. Consult with pharmacist, if available.

Use aseptic technique for single or multiple entry and withdrawal from all containers.

When diluting or dissolving drugs, mix thoroughly and use promptly.

Do not store reconstituted solutions of drugs for injection unless otherwise directed by the manufacturer of the solute.

Do not use unless the solution is clear and seal intact.

ADVERSE REACTIONS

Reactions which may occur because of this solution, added drugs or the technique of reconstitution or administration include febrile response, local tenderness, abscess, tissue necrosis or infection at the site of injection, venous thrombosis or phlebitis extending from the site of injection and extravasation.

If an adverse reaction does occur, discontinue the infusion, evaluate the patient, institute appropriate countermeasures, and if possible, retrieve and save the remainder of the unused vehicle for examination.

Although adverse reactions to intravenous, intramuscular or subcutaneous injection of 0.9% benzyl alcohol are not known to occur in man, experimental studies of small volume parenteral preparations containing 0.9% benzyl alcohol in several species of animals have indicated that an estimated intravenous dose up to 30 mL may be safely given to an adult without toxic effects. Administration of an estimated 9 mL to a 6 kg infant or neonate is potentially capable of producing blood pressure changes.

OVERDOSAGE

Use only as a diluent or solvent. This parenteral preparation is unlikely to pose a threat of fluid overload except possibly in very small infants. In the event these should occur, re-evaluate the patient and institute appropriate corrective measures. See WARNINGS, PRECAUTIONSand ADVERSE REACTIONS.

DOSAGE AND ADMINISTRATION

The volume of the preparation to be used for diluting or dissolving any drug for injection is dependent on the vehicle concentration, dose and route of administration as recommended by the manufacturer.

Parenteral drug products should be inspected visually for particulate matter and discoloration prior to administration, whenever solution and container permit. See PRECAUTIONS.

HOW SUPPLIED

Unit of Sale | Benzyl Alcohol Preservative Concentration
NDC 84549-977-03 Multiple-dose 30 mL plastic Fliptop vial | 9 mg/mL

Store at 20 to 25°C (68 to 77°F). [See USP Controlled Room Temperature.]